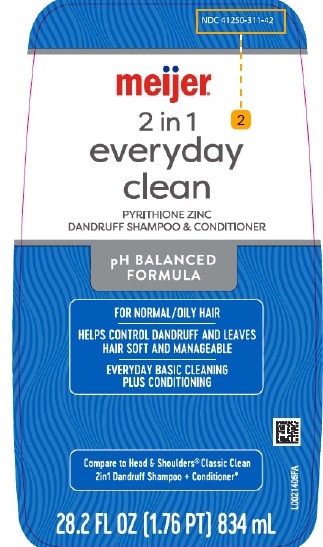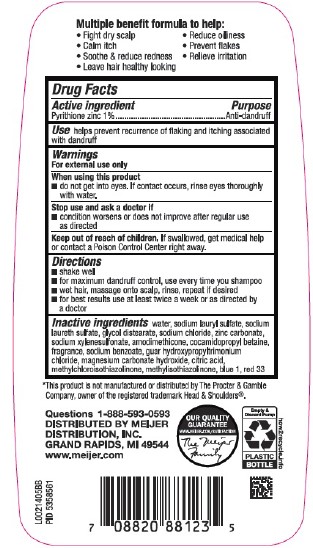 DRUG LABEL: Everyday Clean
NDC: 41250-311 | Form: SHAMPOO
Manufacturer: Meijer, Inc.
Category: otc | Type: HUMAN OTC DRUG LABEL
Date: 20260219

ACTIVE INGREDIENTS: PYRITHIONE ZINC 10 mg/1 mL
INACTIVE INGREDIENTS: WATER; SODIUM LAURYL SULFATE; SODIUM LAURETH SULFATE; GLYCOL DISTEARATE; SODIUM CHLORIDE; ZINC CARBONATE; SODIUM XYLENESULFONATE; AMODIMETHICONE (800 CST); COCAMIDOPROPYL BETAINE; SODIUM BENZOATE; GUAR HYDROXYPROPYLTRIMONIUM CHLORIDE (1.7 SUBSTITUENTS PER SACCHARIDE); MAGNESIUM CARBONATE HYDROXIDE; CITRIC ACID MONOHYDRATE; METHYLCHLOROISOTHIAZOLINONE; METHYLISOTHIAZOLINONE; FD&C BLUE NO. 1; D&C RED NO. 33

Meijer 311.007/311AK-AN
Dandruff Shampoo, Everyday Clean 2 in 1

claims

Multiple benefit formula to help:

- Fight dry scalp
- Calm itch
- Soothe & reduce redness
- Leave hair healthy looking
- Reduce oilness
- Prevent flakes
- Relieve irritation

Active ingredients

Pyrithione zinc 1%

Purpose

Anti-Dandruff

Use

helps prevent recurrence of flaking and itching assoicated with dandruff

Warnings

For external use only

When using this product

- do not get into eyes. If contact occurs, rinse eyes thoroughly with water.

Stop use and ask a doctor

- condition worsens or does not improve after regular use as directed

Keep out of reach of children.

If swallowed, get medical help or contact a Poison Control Center right away.

Directions

- shake well
- for maximum dandruff control, use every time you shampoo
- wet hair, massage onto scalp, rinse, repeat if desired
- for best results use at least twice a week or as directed by a doctor

inactive ingredients

water, sodium lauryl sulfate, sodium laureth sulfate, glycol distearate, sodium chloride, zinc carbonate, sodium xylenesulfonate, amodimethicone, cocamidoporpyl betaine, fragrance, sodium benzoate, guar hydroxypropyltrimonium chloride, magnesium carbonate hydroxide, citric acid, methylchloroisothiazolinone, methylisothiazolinone, blue 1, red 33

Disclaimer

*This product is not manufactured or distributed by The Procter & Gamble Company, owner of the registered trademark Head & Shoulders®.

Adverse reactions

Questions 1-888-593-0593

DISTRIBUTED BY

MEIJER DISTRIBUTION, INC

GRAND RAPIDS, MI 49544

www.meijer.com

OUR QUALITY GUARNATEE

WWW.MEIJER.COM/SATISFACTION

THE MEIJER FAMILY

Empty & Discard Pump

PLASTIC BOTTLE

how2recycle.info

Principal display panel

NDC 41250-311-42

meijer®

2 in 1

everyday

clean

PYRITHIONE ZINC

DANDRUFF SHAMPOO

pH BALANCED FORMULA

For Normal/Oily Hair

Helps control dandruff and leaves hair soft and manageable

Everyday basic cleaning plus conditioning

Compare to Head & Shoulders®2 in 1 Classic Clean Dandruff Shampoo + Conditioner*

28.2 FL OZ (1.76 PT) 834 mL